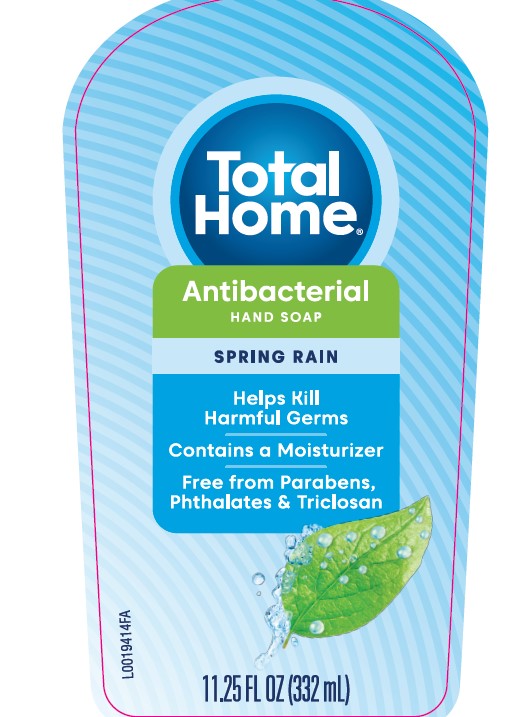 DRUG LABEL: Hand wash
NDC: 69842-383 | Form: SOAP
Manufacturer: CVS Pharmacy
Category: otc | Type: HUMAN OTC DRUG LABEL
Date: 20210125

ACTIVE INGREDIENTS: BENZALKONIUM CHLORIDE 1.3 mg/1 mL
INACTIVE INGREDIENTS: WATER; LAURAMINE OXIDE; COCAMIDOPROPYL BETAINE; LAURAMIDOPROPYLAMINE OXIDE; SODIUM CHLORIDE; MYRISTAMIDOPROPYLAMINE OXIDE; GLYCERIN; DISTEARETH-75 ISOPHORONE DIISOCYANATE; PEG-150 DISTEARATE; CITRIC ACID MONOHYDRATE; EDETATE SODIUM; SULISOBENZONE; SODIUM BENZOATE; FD&C BLUE NO. 1; D&C RED NO. 33

Total Home 942.001 942AB

Active ingredients

Benzalkonium chloride 0.13%

Purpose

Antibacterial

Use

for handwashing to decrease bacteria on the skin

Warnings

For external use only-hands only

When using this product

- avoid contact with eyes. If contact occurs, rinse eyes thoroughly with water.

Stop use and ask a doctor if

- irritation or redness develops
- condition persists for more than 72 hours

Keep out of reach of children

If swallowed, get medical help or contact a Poison Control Center right away.

Directions

- wet hands
- apply palmful to hands
- scrub thoroughly
- rinse thoroughly

Inactive ingredients

water, lauramine oxide, cocamidopropyl betaine, lauramidopropylamine oxide, sodium chloride, myristamidopropylamine oxide, glycerin, fragrance, disteareth-75 IPDI, PEG-150 distearate, citric acid, tetrasodium EDTA, benzophenone-4, sodium benzoate, blue 1, red 33

adverse reaction section

Distributed by: CVS Pharmacy, Inc

One CVS Drive, Woonsocket, RI 02895

©2021 CVS/pharmacy

CVS.com 1-800-Shop CVS

CVS Quality

money back quarantee

principal display panel

Total

Home

Antibacterial

HAND SOAP

SPRING RAIN

Helps Kill Harmful Germs

Contains a Moisturizer

Free from Parabens, Phthalates & Triclosan

11.25 FL OZ (332 mL)